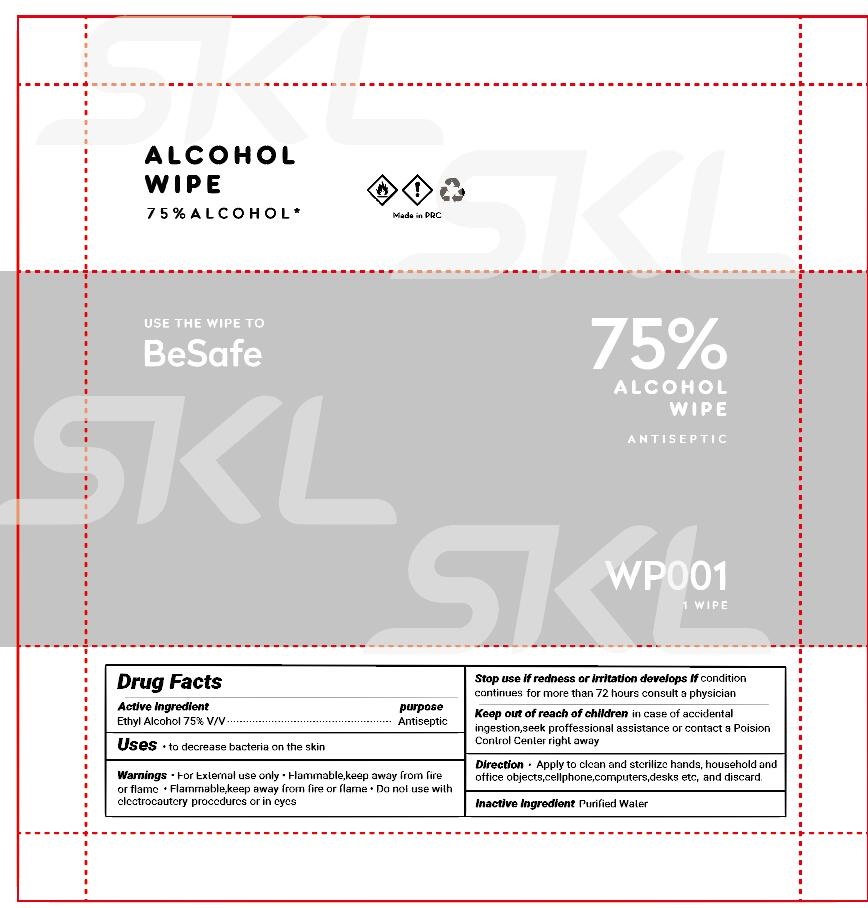 DRUG LABEL: Alcohol Wipe
NDC: 74979-004 | Form: CLOTH
Manufacturer: Robert Gordon Ind. Ltd.
Category: otc | Type: HUMAN OTC DRUG LABEL
Date: 20200928

ACTIVE INGREDIENTS: ALCOHOL 0.75 mL/1 mL
INACTIVE INGREDIENTS: WATER

Alcohol Wipe

Active Ingredient

Ethyl Alcohol 75% (v/v)

purpose

Antiseptic

Uses

- to decrease bacteria on the skin

Warnings

- For External use only
- Flammable,keep away from fire or flame
- Flammable,keep away from fire or flame

Do not use

- with electrocautcry procedures or in eyes

Stop use if redness or irritation develops If

condition continues for more than 72 hours consult a physician

Keep out of reach of children

in case of accidental ingestion,seek proffessional assistance or contact a Poision Control Center right away

Directions

- Apply to clean and sterilizc hands, household and office objects,cellphone, computers,desks etc, and discard.

Inactive ingredient

Purified Water